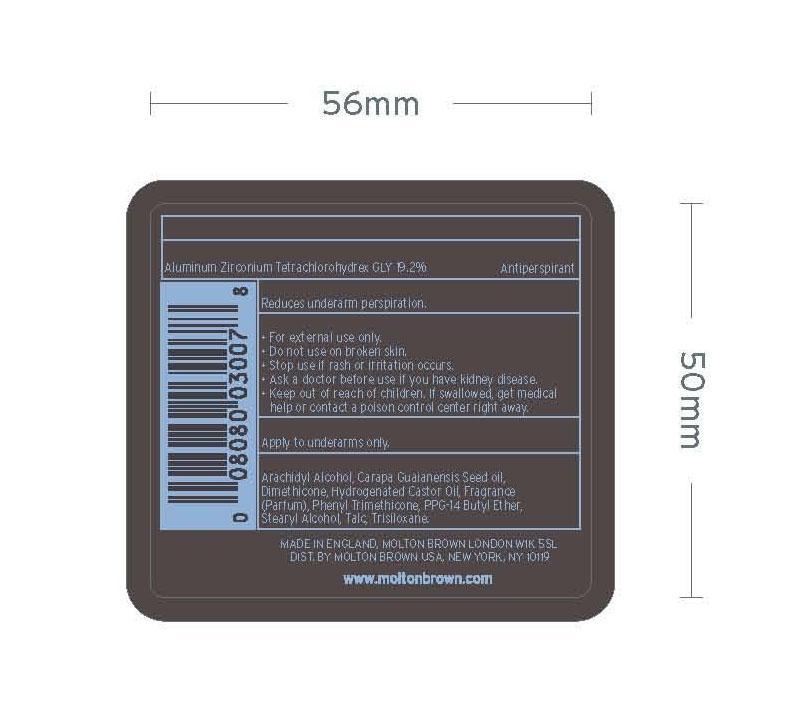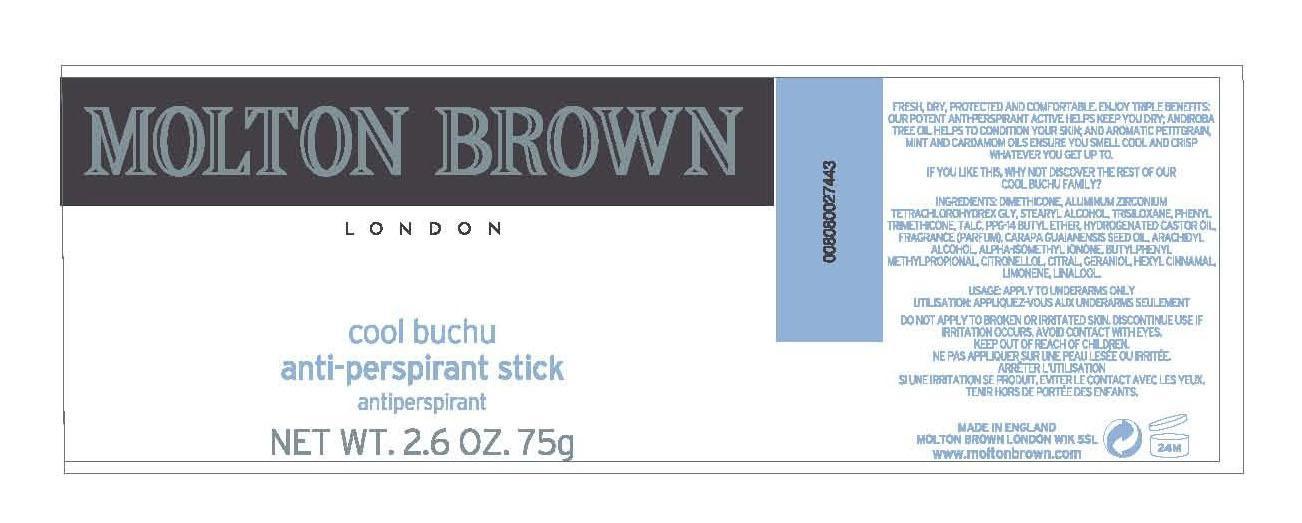 DRUG LABEL: Molton Brown
NDC: 68814-111 | Form: STICK
Manufacturer: Molton Brown Ltd. 
Category: otc | Type: HUMAN OTC DRUG LABEL
Date: 20130130

ACTIVE INGREDIENTS: ALUMINUM ZIRCONIUM TETRACHLOROHYDREX GLY 19.2 g/100 g
INACTIVE INGREDIENTS: ARACHIDYL ALCOHOL; CARAPA GUIANENSIS SEED OIL; DIMETHICONE; HYDROGENATED CASTOR OIL; PHENYL TRIMETHICONE; PPG-14 BUTYL ETHER; STEARYL ALCOHOL; TALC; TRISILOXANE

Cool Buchu Anti-Perspirant

Active Ingredients Purpose
Aluminum Zirconium Tetrachlorohydrex Gly 19.2% Antiperspirant

PURPOSE

Reduces underarm perspiration

Keep out of reach of children. If swallowed, get medical help or contact a poison control center right away.

INDICATIONS AND USAGE

For external use only.

Do not use on broken skin
Stop use if rash or irritation occurs

Ask a doctor before use if you have kidney disease

DOSAGE AND ADMINISTRATION

Apply to underarm only

INACTIVE INGREDIENT

Archidyl Alcohol, Carapa Guaianensis Seed Oil, Dimethicone, Hydrogenated Castor Oil, Fragrance (Parfum), Phenyl Trimethicone, PPG-14 Butyl Ether, Stearyl Alcohol, Talc, Trisiloxane

PACKAGE LABEL

Molton Brown London
Cool Buchu
Anti-Perspirant Stick
antiperspirant stick